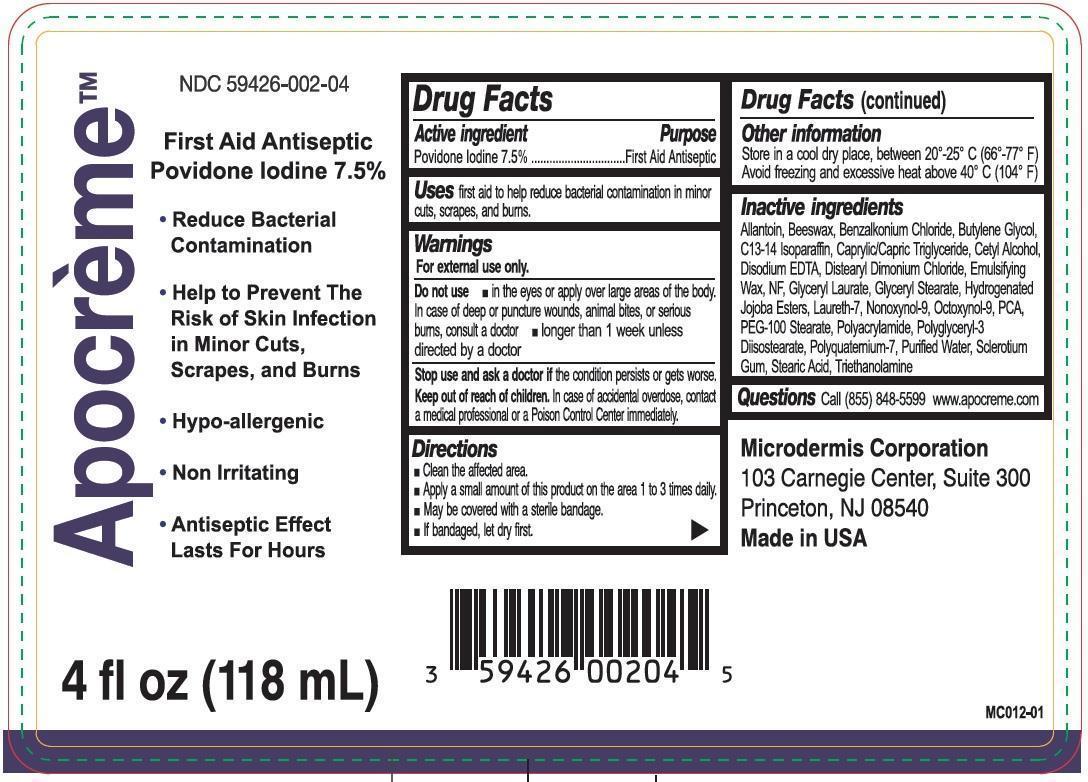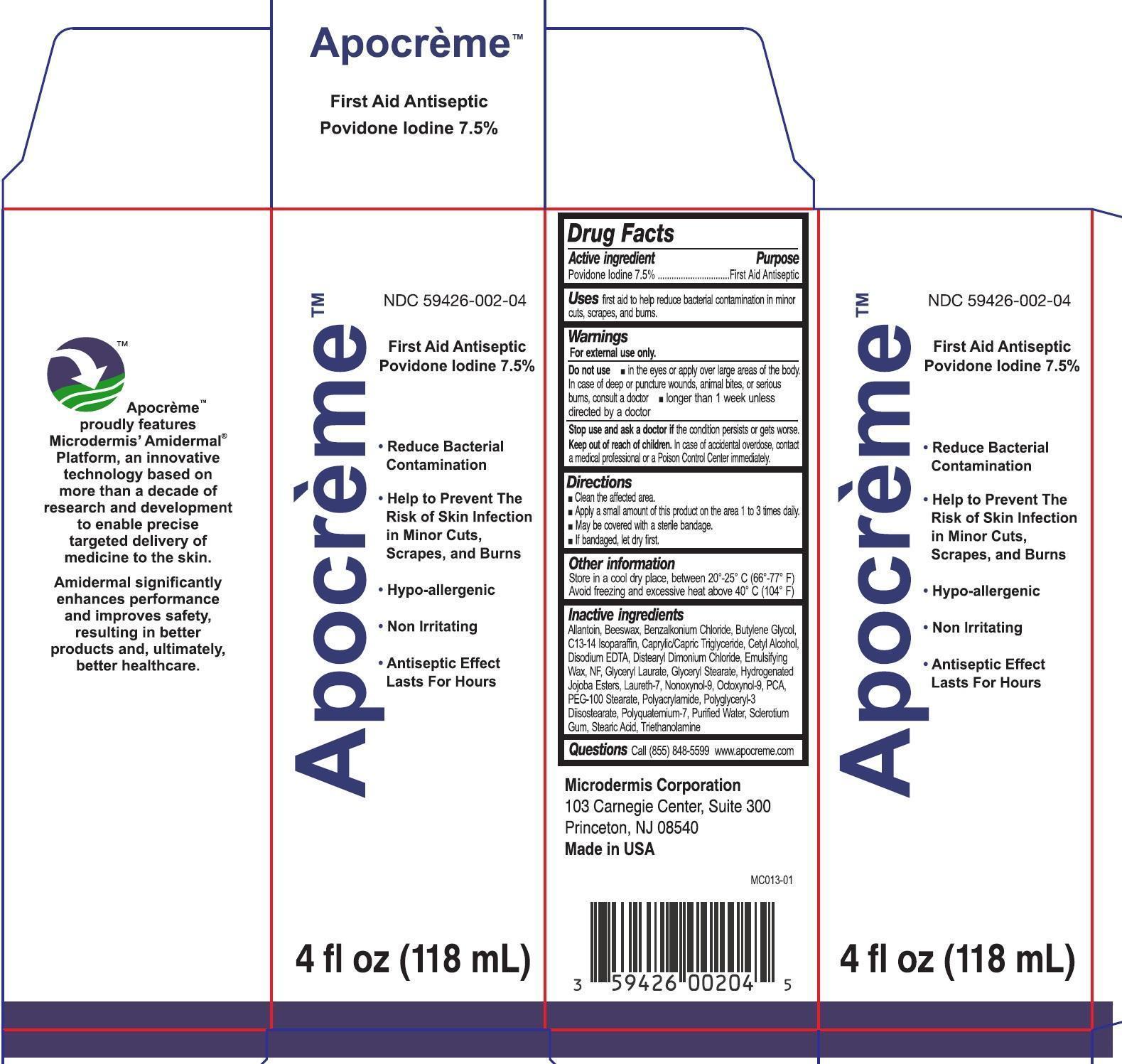 DRUG LABEL: Apocreme
NDC: 59426-002 | Form: EMULSION
Manufacturer: Microdermis Corporation
Category: otc | Type: HUMAN OTC DRUG LABEL
Date: 20150621

ACTIVE INGREDIENTS: POVIDONE-IODINE 75 mg/1 mL
INACTIVE INGREDIENTS: ALLANTOIN; YELLOW WAX; BENZALKONIUM CHLORIDE; BUTYLENE GLYCOL; C13-14 ISOPARAFFIN; MEDIUM-CHAIN TRIGLYCERIDES; CETYL ALCOHOL; EDETATE DISODIUM; DISTEARYLDIMONIUM CHLORIDE; GLYCERYL LAURATE; GLYCERYL MONOSTEARATE; LAURETH-7; NONOXYNOL-9; OCTOXYNOL-9; PIDOLIC ACID; PEG-100 STEARATE; POLYGLYCERYL-3 DIISOSTEARATE; WATER; BETASIZOFIRAN; STEARIC ACID; TROLAMINE

Apocreme

Active ingredient

Povidone Iodine 7.5%

Purpose

First Aid Antiseptic

Uses

First aid to help reduce bacterial contamination in minor cuts, scrapes, and burns

Warnings

For external use only.

Do not use

- In the eyes or apply over large areas of the body. In case of deep or puncture wounds, animals bites, or serious burns, consult a doctor
- Longer than 1 week unless directed by a doctor

Stop use and ask a doctor

If the condition persists or gets worse.

Keep out of reach of children.

In case of accidental overdose, contact a medical professional or a Poison Control Center immediately.

Directions

- Clean the affected area.
- Apply a small amount of this product on the area 1 to 3 times daily.
- May be coveres with a sterile bandage.
- If bandaged, let dry first.

Other information

Store in a cool dry place, between 20o-25o C (66o -77o F)

Avoid freezing and excessive heat above 40o C (104o F)

Inactive ingredients

Allantoin, Beeswax, Benzalkonium Chloride, Butylene Glycol, C13-14 Isoparaffin, Caprylic/Capric Triglyceride, Cetyl Alcohol, Disodium EDTA, Distearyl Dimonium Chloride, Emulsifying Wax, NF, Glyceryl Laurate, Glyceryl Stearate, Hydeogenated Jojoba Esters, Laureth-7, Nonoxynol-9, Octoxynol-9, PCA, PEG-100 Stearate, Polyacrylamide, Polyglyceryl-3 Diisostearate, Polyquatemium-7, Purified Water, Sclerotium Gum, Stearic Acid, Triethanolamine

Questions

Call (855) 848-5599 www.apocreme.com